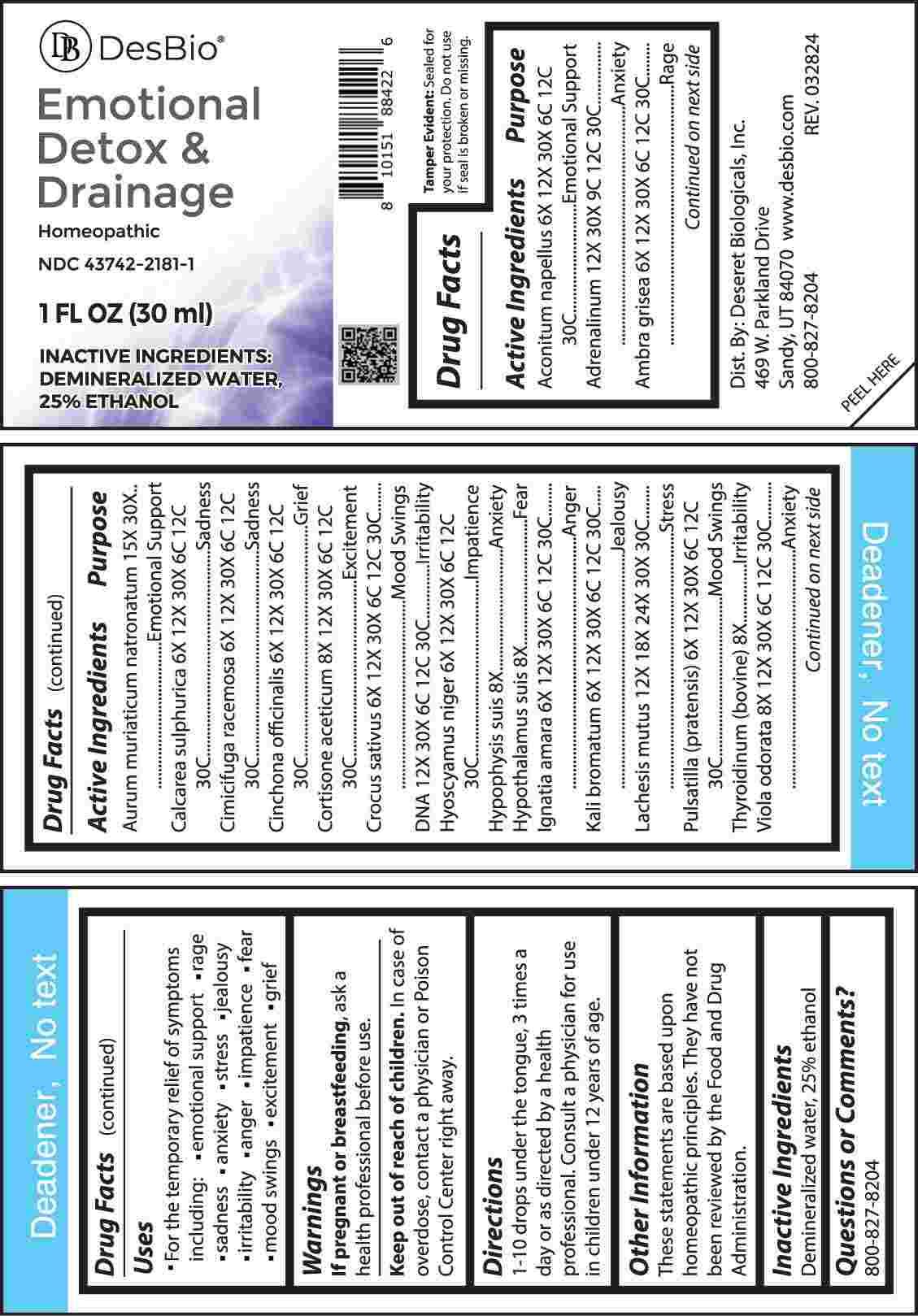 DRUG LABEL: Emotional Detox and Drainage
NDC: 43742-2181 | Form: LIQUID
Manufacturer: Deseret Biologicals, Inc.
Category: homeopathic | Type: HUMAN OTC DRUG LABEL
Date: 20240813

ACTIVE INGREDIENTS: ACONITUM NAPELLUS WHOLE 6 [hp_X]/1 mL; EPINEPHRINE 12 [hp_X]/1 mL; AMBERGRIS 6 [hp_X]/1 mL; SODIUM TETRACHLOROAURATE 15 [hp_X]/1 mL; CALCIUM SULFATE ANHYDROUS 6 [hp_X]/1 mL; BLACK COHOSH 6 [hp_X]/1 mL; CINCHONA OFFICINALIS BARK 6 [hp_X]/1 mL; CORTISONE ACETATE 8 [hp_X]/1 mL; SAFFRON 6 [hp_X]/1 mL; HERRING SPERM DNA 12 [hp_X]/1 mL; HYOSCYAMUS NIGER 6 [hp_X]/1 mL; SUS SCROFA PITUITARY GLAND 8 [hp_X]/1 mL; SUS SCROFA HYPOTHALAMUS 8 [hp_X]/1 mL; STRYCHNOS IGNATII SEED 6 [hp_X]/1 mL; POTASSIUM BROMIDE 6 [hp_X]/1 mL; LACHESIS MUTA VENOM 12 [hp_X]/1 mL; PULSATILLA PRATENSIS WHOLE 6 [hp_X]/1 mL; THYROID, BOVINE 8 [hp_X]/1 mL; VIOLA ODORATA WHOLE 8 [hp_X]/1 mL
INACTIVE INGREDIENTS: WATER; ALCOHOL

DRUG FACTS:

ACTIVE INGREDIENTS:

Aconitum Napellus 6X, 12X, 30X, 6C, 12C, 30C, Adrenalinum 12X, 30X, 9C, 12C, 30C, Ambra Grisea 6X, 12X, 30X, 6C, 12C, 30C, Aurum Muriaticum Natronatum 15X, 30X, Calcarea Sulphurica 6X, 12X, 30X, 6C, 12C, 30C, Cimicifuga Racemosa 6X, 12X, 30X, 6C, 12C, 30C, Cinchona Officinalis 6X, 12X, 30X, 6C, 12C, 30C, Cortisone Aceticum 8X, 12X, 30X, 6C, 12C, 30C, Crocus Sativus 6X, 12X, 30X, 6C, 12C, 30C, DNA 12X, 30X, 6C, 12C, 30C, Hyoscyamus Niger 6X, 12X, 30X, 6C, 12C, 30C, Hypophysis Suis 8X, Hypothalamus Suis 8X, Ignatia Amara 6X, 12X, 30X, 6C, 12C, 30C, Kali Bromatum 6X, 12X, 30X, 6C, 12C, 30C, Lachesis Mutus 12X, 18X, 24X, 30X, 30C, Pulsatilla (Pratensis) 6X, 12X, 30X, 6C, 12C, 30C, Thyroidinum (Bovine) 8X, Viola Odorata 8X, 12X, 30X, 6C, 12C, 30C.

PURPOSE:

Aconitum Napellus – Emotional Support, Adrenalinum - Anxiety, Ambra Grisea - Rage, Aurum Muriaticum Natronatum – Emotional Support, Calcarea Sulphurica - Sadness, Cimicifuga Racemosa - Sadness, Cinchona Officinalis - Grief, Cortisone Aceticum – Excitement, Crocus Sativus – Mood Swings, DNA - Irritability, Hyoscyamus Niger - Impatience, Hypophysis Suis - Anxiety, Hypothalamus Suis - Fear, Ignatia Amara - Anger, Kali Bromatum - Jealousy, Lachesis Mutus - Stress, Pulsatilla (Pratensis) – Mood Swings, Thyroidinum (Bovine) - Irritability, Viola Odorata - Anxiety

USES:

• For the temporary relief of symptoms including:

• emotional support • rage • sadness • anxiety

• stress • jealousy • irritability • anger • impatience

• fear • mood swings • excitement • grief

These statements are based upon homeopathic principles. They have not been reviewed by the Food and Drug Administration.

WARNINGS:

If pregnant or breast-feeding, ask a health professional before use.

Keep out of reach of children. In case of overdose, contact a physician or Poison Control Center right away.

Tamper Evident: Sealed for your protection. Do not use if seal is broken or missing.

KEEP OUT OF REACH OF CHILDREN:

In case of overdose, contact a physician or Poison Control Center right away.

DIRECTIONS:

1-10 drops under the tongue, 3 times a day or as directed by a health professional. Consult a physician for use in children under 12 years of age.

INACTIVE INGREDIENTS:

Demineralized water, 25% ethanol

QUESTIONS:

Dist. By: Deseret Biologicals, Inc.

469 W. Parkland Drive

Sandy, UT 84070

www.desbio.com

800-827-8204

PACKAGE LABEL DISPLAY:

DesBio

Emotional Detox

& Drainage

Homeopathic

NDC 43742-2181-1

1 FL OZ (30 ml)